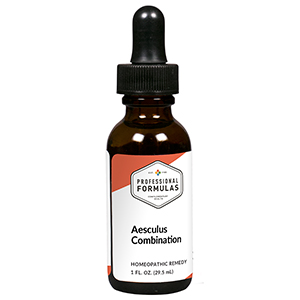 DRUG LABEL: Aesculus Combination
NDC: 63083-9202 | Form: LIQUID
Manufacturer: Professional Complementary Health Formulas
Category: homeopathic | Type: HUMAN OTC DRUG LABEL
Date: 20190815

ACTIVE INGREDIENTS: HORSE CHESTNUT 1 [hp_X]/29.5 mL; ECHINACEA ANGUSTIFOLIA WHOLE 2 [hp_X]/29.5 mL; ARNICA MONTANA WHOLE 3 [hp_X]/29.5 mL; CLAVICEPS PURPUREA SCLEROTIUM 3 [hp_X]/29.5 mL; AVISCUMINE 3 [hp_X]/29.5 mL; APIS MELLIFERA 4 [hp_X]/29.5 mL; BAPTISIA TINCTORIA WHOLE 4 [hp_X]/29.5 mL; BENZOIC ACID 4 [hp_X]/29.5 mL; COLCHICUM AUTUMNALE BULB 4 [hp_X]/29.5 mL; HAMAMELIS VIRGINIANA ROOT BARK/STEM BARK 4 [hp_X]/29.5 mL; RUTA GRAVEOLENS FLOWERING TOP 4 [hp_X]/29.5 mL; BARIUM IODIDE 6 [hp_X]/29.5 mL; EUPATORIUM PERFOLIATUM FLOWERING TOP 6 [hp_X]/29.5 mL; TOXICODENDRON PUBESCENS LEAF 6 [hp_X]/29.5 mL; SOLANUM NIGRUM TOP 6 [hp_X]/29.5 mL; SODIUM PYRUVATE 8 [hp_X]/29.5 mL; BEEF HEART 10 [hp_X]/29.5 mL; TOBACCO LEAF 10 [hp_X]/29.5 mL; COPPER 13 [hp_X]/29.5 mL; SULFUR 30 [hp_X]/29.5 mL
INACTIVE INGREDIENTS: ALCOHOL; WATER

R202

ACTIVE INGREDIENTS

Aesculus hippocastanum 1X
Echinacea angustifolia 2X
Arnica montana 3X
Secale cornutum 3X
Viscum album 3X
Apis mellifica 4X
Baptisia tinctoria 4X
Benzoicum acidum 4X
Colchicum autumnale 4X
Hamamelis virginiana 4X
Ruta graveolens 4X
Baryta iodata 6X
Eupatorium perfoliatum 6X
Rhus toxicodendron 6X
Solanum nigrum 6X
Natrum pyruvicum 8X
Arteria 10X
Tabacum 10X
Cuprum metallicum 13X
Sulphur 30X

QUESTIONS

Professional Formulas

PO Box 2034 Lake Oswego, OR 97035

INDICATIONS

For the temporary relief of occasional constipation, sluggish digestion, minor joint pain or swelling, or sporadic leg pain, particularly when walking.*

PURPOSE

*Claims based on traditional homeopathic practice, not accepted medical evidence. Not FDA evaluated.

WARNINGS

In case of overdose, get medical help or contact a poison control center right away.

Keep out of the reach of children.

PREGNANCY OR BREAST FEEDING

If pregnant or breastfeeding, ask a healthcare professional before use.

DIRECTIONS

Place drops under tongue 30 minutes before/after meals. Adults and children 12 years and over: Take 10 drops up to 3 times per day. Consult a physician for use in children under 12 years of age.

OTHER INFORMATION

Tamper resistant. If seal is broken, do not use. After opening, close container tightly and store at room temperature away from heat.

INACTIVE INGREDIENTS

40% ethanol, purified water.

LABEL

Est 1985

Professional Formulas

Complementary Health

Aesculus Combination

Homeopathic Remedy

1 FL. OZ. (29.5 mL)